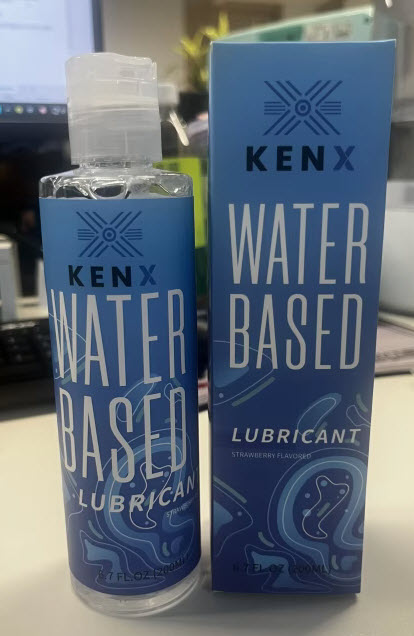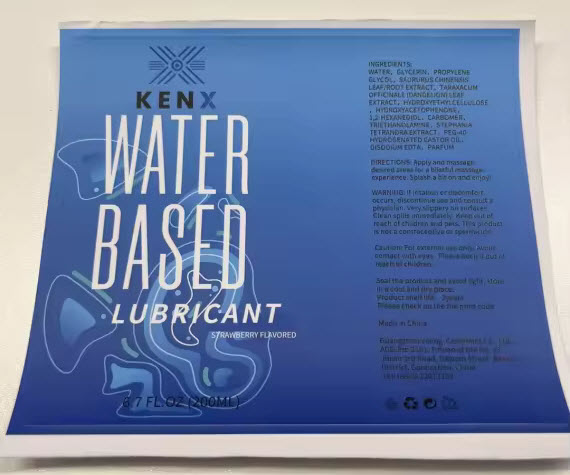 DRUG LABEL: KENX WATER BASED PERSONAL LUBRICANT
NDC: 85280-800 | Form: OIL
Manufacturer: SB Innovations LLC
Category: otc | Type: HUMAN OTC DRUG LABEL
Date: 20250221

ACTIVE INGREDIENTS: HYDROXYETHYLCELLULOSE 6.7 g/200 mL
INACTIVE INGREDIENTS: PEG-40 HYDROGENATED CASTOR OIL; SAURURUS CHINENSIS WHOLE; 2'-HYDROXYACETOPHENONE; 1,2-HEXANEDIOL; TRIETHANOLAMINE; PARFUMIDINE; GLYCERIN; PROPYLENE GLYCOL 1,2-DISTEARATE; STEPHANIA TETRANDRA WHOLE; MAGNESIUM DISODIUM EDTA; WATER; TARAXACUM OFFICINALE (DANDELION) ROOT; CARBOMER

INDICATIONS AND USAGE

Apply and massage desired areas for a bilssful massage experience. Splash a bit on and enjoy!

WARNINGS

If iritation or discomfort occurs, discontinue use and consult a physician.

Very slippery on surfaces.

Clean spills immediately.

Keep out of reach of children and pets.

This product is not a contraceptive or spermicide.

WARNINGS AND PRECAUTIONS

Caution: For external use only. Avoid contact with eyes. please keep it out of rach of children.

STORAGE AND HANDLING

Seal the product and avoid light. Store in a cool and dry place.

Product shelf life: 3 years

Please check on the print code.

DOSAGE AND ADMINISTRATION

6.7 FL.OZ (200ML)

Keep out of reach of children and pets.

PURPOSE

Gently squeeze out an appropriate amount of lubricant, and evenly apply it on the desired area.

ACTIVE INGREDIENT

HYDROXYETHYL CELLULOSE

INACTIVE INGREDIENT

Water, Glycerin, Propylence Glycol, Saururus Chinensis Leaf/Root Extract, Taraxacum Officinale (Dandelion) Leaf Extract, Hydroxyethylcellulose, Hydroxyacetophenone, 1,2-Hexanediol, Carbomer, Triethanolamine, Stephania Tetrandra Extract, PEG-40 Hydrogenated Castor Oil, Disodum Edta, Parfum